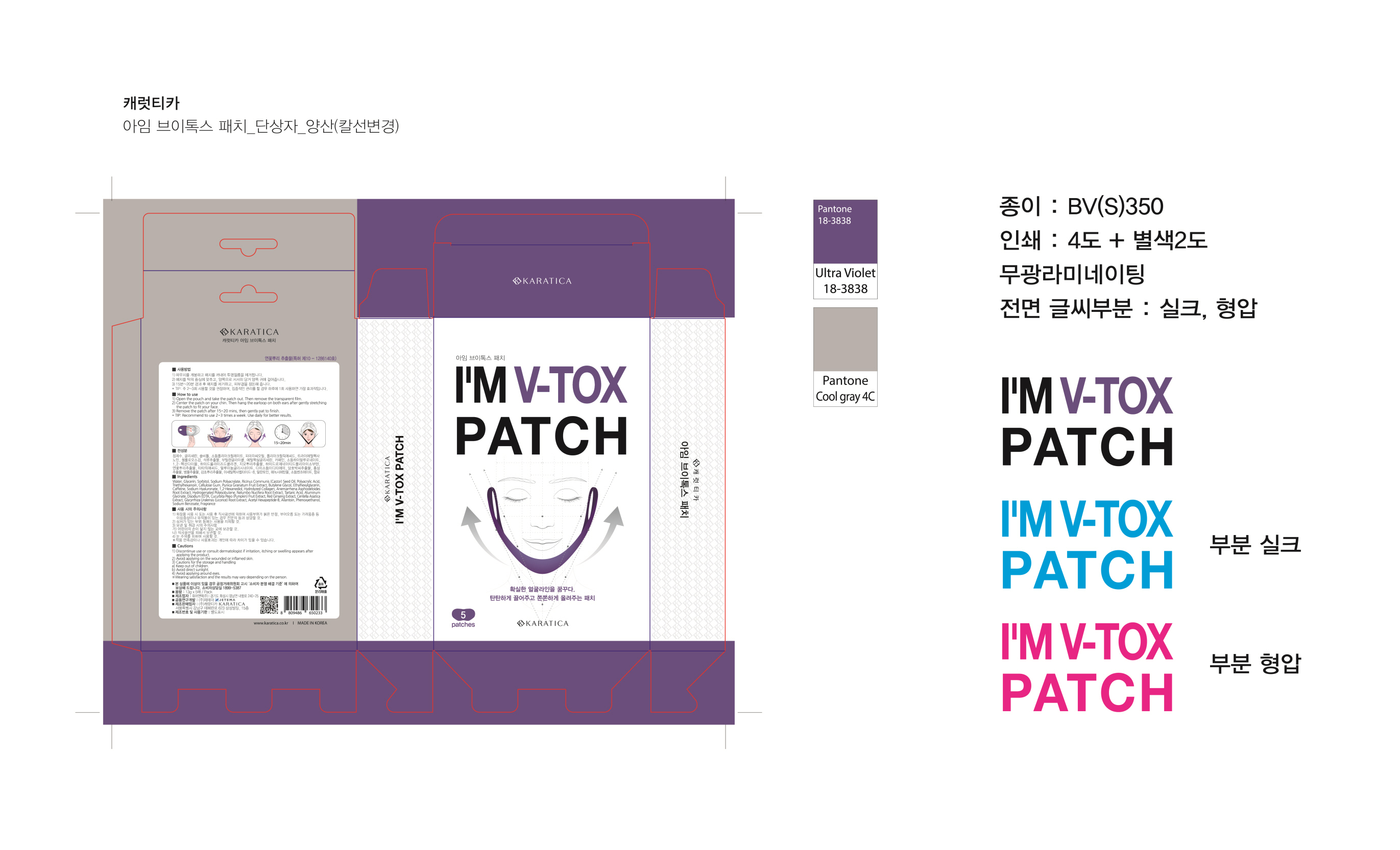 DRUG LABEL: Im V-Tox
NDC: 70514-0011 | Form: PATCH
Manufacturer: Karatica Co., Ltd
Category: otc | Type: HUMAN OTC DRUG LABEL
Date: 20180315

ACTIVE INGREDIENTS: GLYCERIN 20 g/100 g
INACTIVE INGREDIENTS: ALLANTOIN; WATER

ACTIVE INGREDIENT

Glycerin

INACTIVE INGREDIENT

Water, Allantoin, Lotus Root Extract, Red Ginseng, etc.

PURPOSE

Multi Function - Lifting, Slimming

keep out or reach of the children

INDICATIONS AND USAGE

1) Open the pouch and take the patch out. Then remove the transparent film.

2) Center the patch on your chin. Then hang the earloop on both ears after gently stretching the patch to fit your face.

3) Remove the patch after 15~20 mins, then gently pat to finish.

*Tip: Recommend to use 2~3 times a week. Use daily for better results.

WARNINGS

1) Discontinue use or consult dermatologist if irritation, itching or swelling appears after applying the product.

2) Avoid applying patches on the wounded, inflamed skin.

3) Cautions for the storage and handling

a) Keep out of children.

B) Avoid direct sunlight.

c) Avoid applying around eyes.

* Wearing satisfaction and the results may vary depending on the person.

DOSAGE AND ADMINISTRATION

for external use only